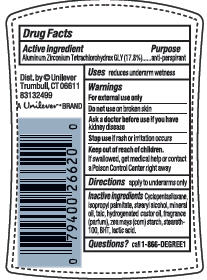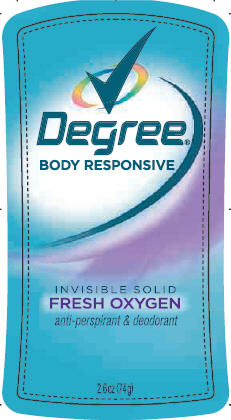 DRUG LABEL: Degree Fresh Oxygen
NDC: 64942-0831 | Form: STICK
Manufacturer: Conopco Inc. d/b/a Unilever
Category: otc | Type: HUMAN OTC DRUG LABEL
Date: 20100616

ACTIVE INGREDIENTS: Aluminum Zirconium Tetrachlorohydrex GLY 17.8 g/100 g

Degree Fresh Oxygen Antiperspirant and Deodorant PDP and drug facts

Active ingredient Purpose

Aluminum Zirconium Tetrachlorohydrex GLY(17.8%)............anti-perspirant

Warning
For external use only

Do not use on broken skin

Ask a doctor before use if you have kidney disease

Stop use if rash or irritation occurs

Keep out of reach of children. If swallowed, get medical help or contact a Poison Control Center right away.

Inactive ingredients

Cyclopentasiloxane, Isopropyl Palmitate, Stearyl Alcohol, Mineral Oil, Talc, Hydrogenated Castor Oil, Fragrance (Parfum), Zea Mays (Corn) Starch, Steareth-100, BHT, Lactic Acid.

Questions? Call toll-free 1-866-DEGREE1

PACKAGE LABEL

PDP 2.6 oz front

PACKAGE LABEL

PDP 2.6 oz back